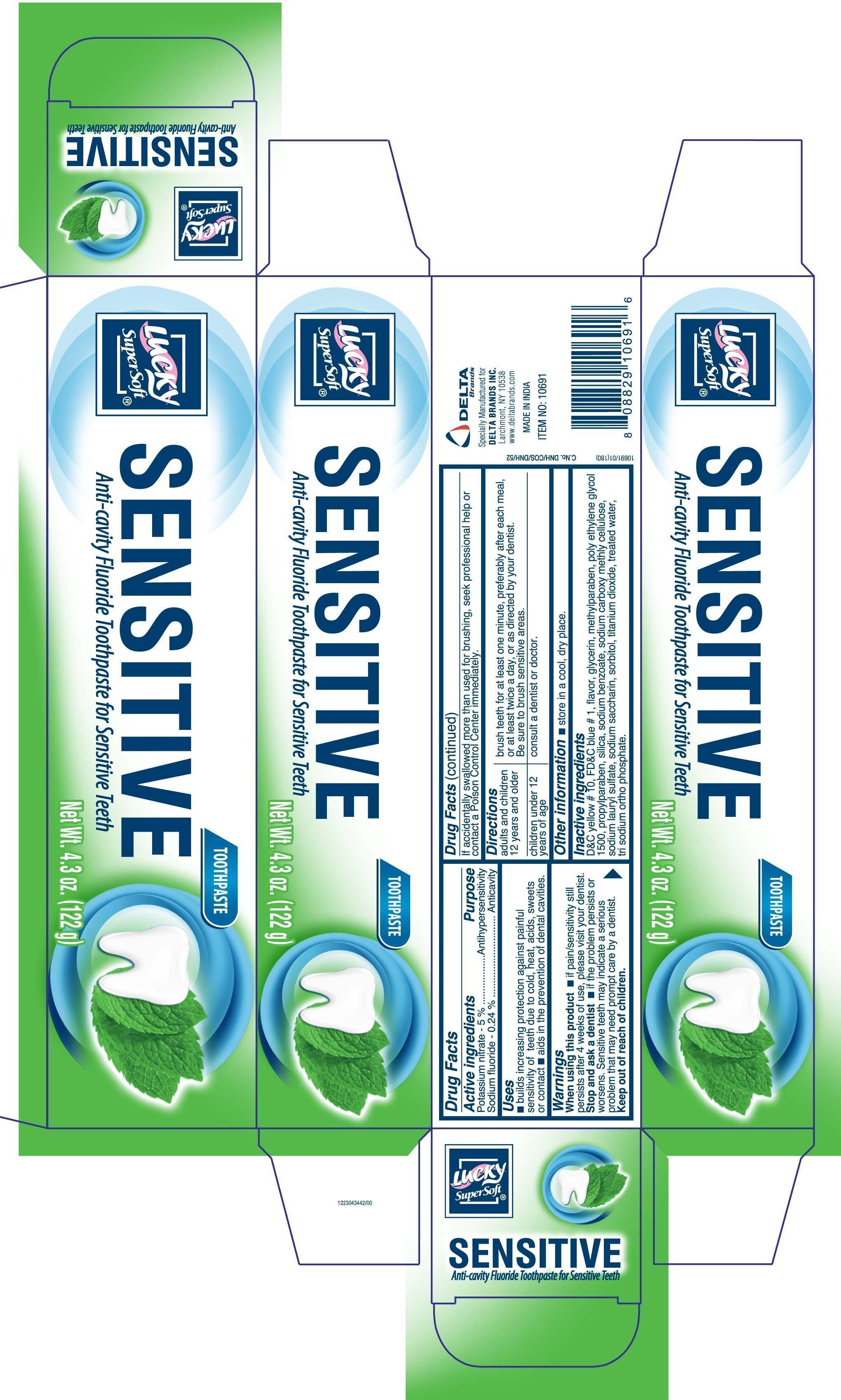 DRUG LABEL: Lucky Super Soft
NDC: 20276-550 | Form: PASTE, DENTIFRICE
Manufacturer: Delta Brands Inc
Category: otc | Type: HUMAN OTC DRUG LABEL
Date: 20170707

ACTIVE INGREDIENTS: POTASSIUM NITRATE 50 mg/1 g; SODIUM FLUORIDE 2.4 mg/1 g
INACTIVE INGREDIENTS: FD&C BLUE NO. 1; GLYCERIN; METHYLPARABEN; POLYETHYLENE GLYCOL 1500; PROPYLPARABEN; SILICON DIOXIDE; SODIUM BENZOATE; CARBOXYMETHYLCELLULOSE SODIUM; SODIUM LAURYL SULFATE; SACCHARIN SODIUM; SORBITOL; TITANIUM DIOXIDE; D&C YELLOW NO. 10; SODIUM PHOSPHATE, TRIBASIC, DODECAHYDRATE; WATER

Drug Facts

Active Ingredient

Potassium nitrate - 5%

Sodium fluoride - 0.24%

Purpose

Antihypersensitivity

Anticavity

Uses

■ builds increasing protection against painful sensitivity of teeth due to cold, heat, acids, sweets or contact ■ aids in the prevention of dental cavities

Warnings

When using this product ■ if pain/sensitivity still persists after 4 weeks of use please visit your dentist

Stop and ask a dentist

■ if problem the persists or worsens. Sensitive teeth may indicate a serious problem that may need prompt care by a dentist.

Keep out of reach of children

If you accidentally swallowed more than used for brushing, seek professional help or contact a Poison Control Center immediately

Directions

adults and children 12 years and older brush teeth for at least one minute, preferably after each meal, or at least twice a day, or as directed by your dentist. Be sure to brush sensitive areas

children under 12 years of age consult a dentist or doctor.

Inactive ingredients

DC Yellow10, FDC Blue 1, flavor, glycerin, methylparaben, poly ethylene glycol 1500, propylparaben, silica, sodium benzoate, sodium carboxy methyl cellulose, sodium lauryl sulfate, sodium saccharin, sorbitol, titanium dioxide, treated water, tri sodium ortho phosphate